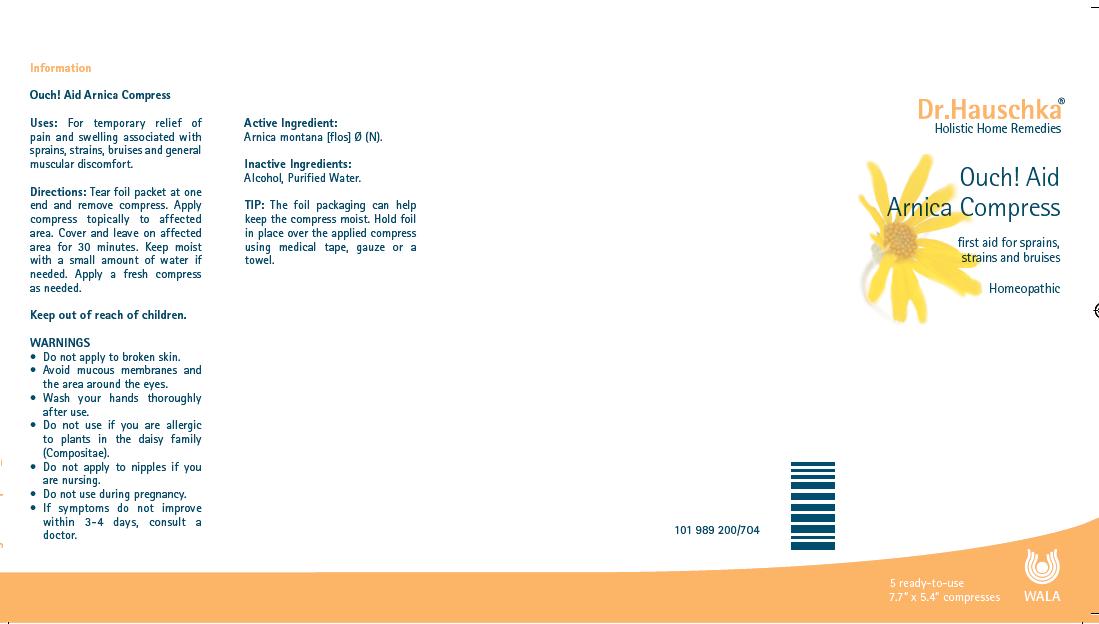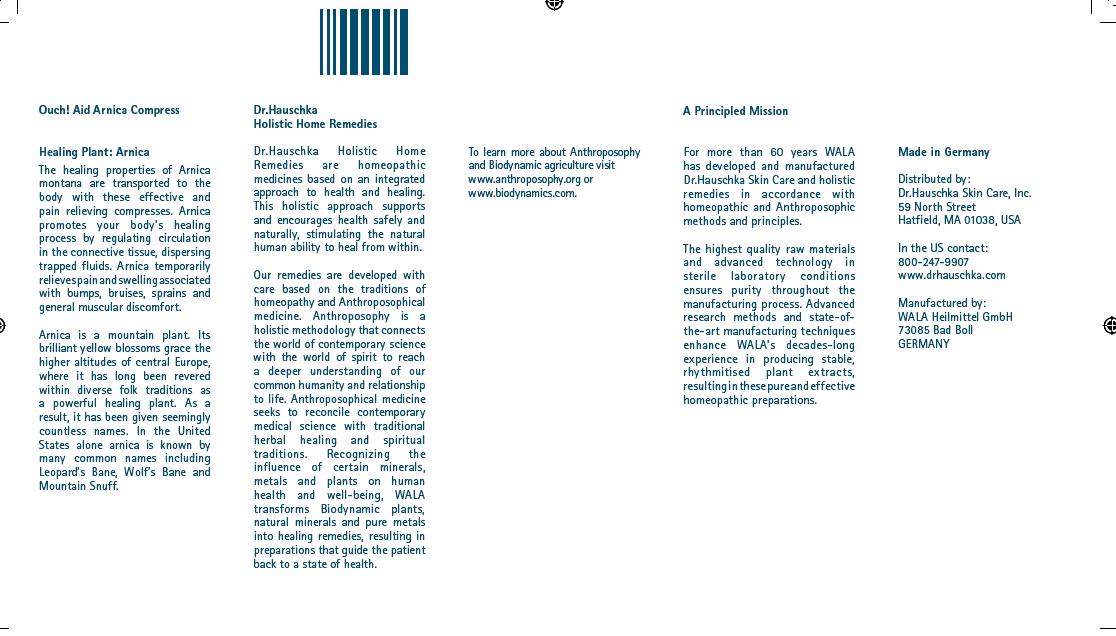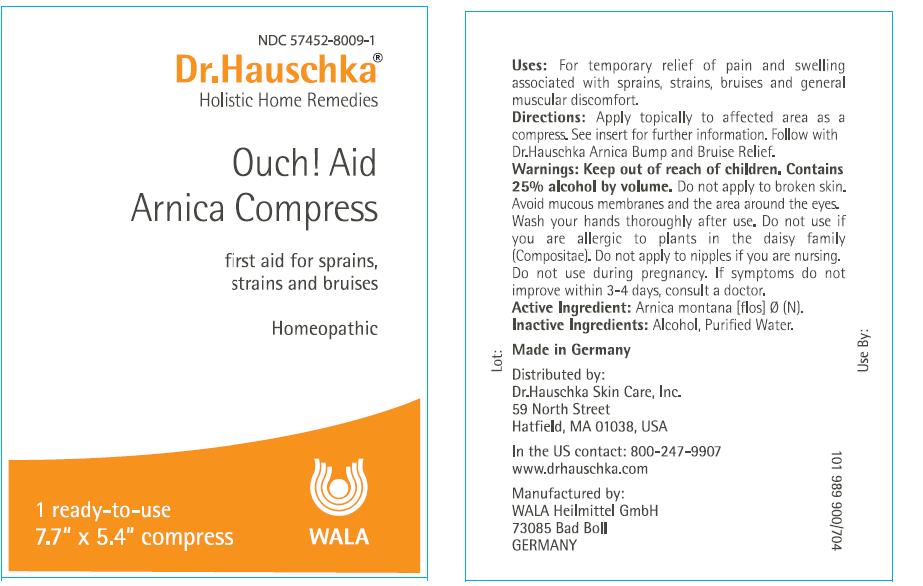 DRUG LABEL: Ouch Aid 
NDC: 51979-001 | Form: TINCTURE
Manufacturer: Dr. Hauschka SkinCare Inc.
Category: homeopathic | Type: HUMAN OTC DRUG LABEL
Date: 20100921

ACTIVE INGREDIENTS: ARNICA MONTANA 4 g/1 1
INACTIVE INGREDIENTS: ALCOHOL; WATER

Active Ingredient: Arnica montana

Inactive Ingredients: Alcohol, Purified Water

PURPOSE

first aid for sprains, strains and bruises

WARNINGS

Contains 25% alcohol by volume. Do not apply to broken skin. Avoid mucous membranes and the area around the eyes. Wash your hands thoroughly after use. Do not use if you are allergic to plants in the daisy family (Compositae).

Keep out of reach of children.

PREGNANCY OR BREAST FEEDING

Do not apply to nipples if you are nursing. Do not use during pregnancy.

ASK DOCTOR

If symptoms do not improve within 3-4 days, consult a doctor.

INDICATIONS AND USAGE

Uses: For temporary relief of pain and swelling associated with sprains, strains, bruises and general muscular discomfort.

DOSAGE AND ADMINISTRATION

Directions: Apply topically to affected area as a compress. See insert for further information. Follow with Dr. Hauschka Arnica Bump and Bruise Relief.

DESCRIPTION

Made in Germany

Distributed By:
Dr. Hauschka Skin Care, Inc.
59 North Street
Hatfield MA 01038, USA

In the US contact: 800-247-9907
www.drhauschka.com

Manufactured by:
WALA Heilmittel GmbH
73085 Bad Boll
Germany

PACKAGE LABEL

Ouch! Aid

Arnica Compress

first aid for sprains, strains and bruises

Homeopathic